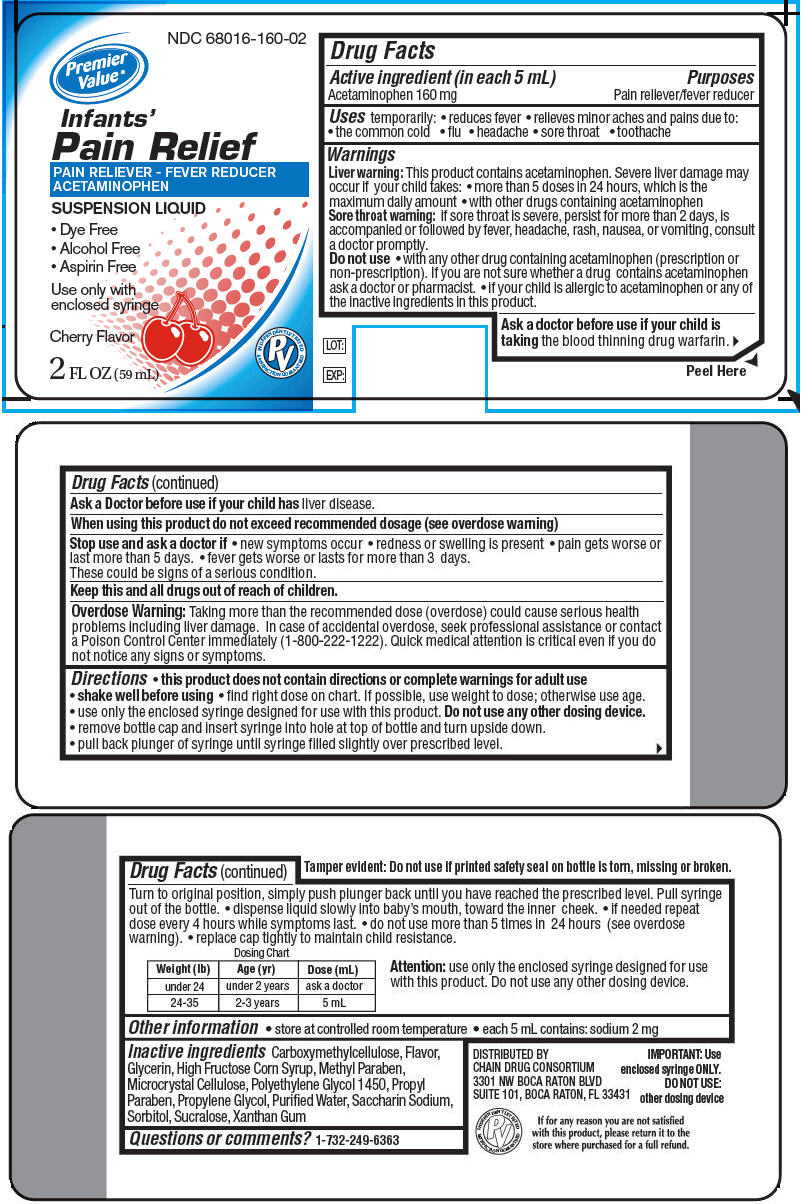 DRUG LABEL: Infants Pain Relief
NDC: 68016-160 | Form: LIQUID
Manufacturer: Chain Drug Consortium (Premier Value)
Category: otc | Type: HUMAN OTC DRUG LABEL
Date: 20141028

ACTIVE INGREDIENTS: Acetaminophen 160 mg/5 mL
INACTIVE INGREDIENTS: Xanthan Gum; Carboxymethylcellulose; Cellulose, Microcrystalline; Methylparaben; Propylparaben; Sucralose; Saccharin Sodium; Propylene Glycol; Polyethylene Glycol 1450; High Fructose Corn syrup; Glycerin; Sorbitol; Water

Infant's Pain Relief

Drug Facts

Active ingredient (in each 5 mL)

Acetaminophen 160 mg

Purposes

Pain reliever/fever reducer

Uses

temporarily:

- reduces fever
- relieves minor aches and pains due to:
  - the common cold
  - flu
  - headache
  - sore throat
  - toothache

Warnings

Liver warning

This product contains acetaminophen. Severe liver damage may occur if your child takes:

- more than 5 doses in 24 hours, which is the maximum daily amount
- with other drugs containing acetaminophen

Sore throat warning: if sore throat is severe, persist for more than 2 days, is accompanied or followed by fever, headache, rash, nausea, or vomiting, consult a doctor promptly.

Do not use

- with any other drug containing acetaminophen (prescription or non-prescription). If you are not sure whether a drug contains acetaminophen ask a doctor or pharmacist.
- if your child is allergic to acetaminophen or any of the inactive ingredients in this product.

Ask a doctor before use if your child is taking the blood thinning drug warfarin.

Ask a Doctor before use if your child has liver disease.

When using this product do not exceed recommended dosage (see overdose warning)

Stop use and ask a doctor if

- new symptoms occur
- redness or swelling is present
- pain gets worse or last more than 5 days.
- fever gets worse or lasts for more than 3 days.

These could be signs of a serious condition.

KEEP OUT OF REACH OF CHILDREN

Keep this and all drugs out of reach of children.

Overdose Warning

Taking more than the recommended dose (overdose) could cause serious health problems including liver damage. In case of accidental overdose, seek professional assistance or contact a Poison Control Center immediately (1-800-222-1222). Quick medical attention is critical even if you do not notice any signs or symptoms.

Directions

- this product does not contain directions or complete warnings for adult use
- shake well before using
- find right dose on chart. If possible, use weight to dose; otherwise use age.
- use only the enclosed syringe designed for use with this product. Do not use any other dosing device.
- remove bottle cap and insert syringe into hole at top of bottle and turn upside down.
- pull back plunger of syringe until syringe filled slightly over prescribed level.

Turn to original position, simply push plunger back until you have reached the prescribed level. Pull syringe out of the bottle.

- dispense liquid slowly into baby's mouth, toward the inner cheek.
- if needed repeat dose every 4 hours while symptoms last.
- do not use more than 5 times in 24 hours (see overdose warning).
- replace cap tightly to maintain child resistance.

Dosing Chart
Weight (lb) | Age (yr) | Dose (mL)
under 24 | under 2 years | ask a doctor
24-35 | 2-3 years | 5 mL

Attention: use only the enclosed syringe designed for use with this product. Do not use any other dosing device.

Other information

- store at controlled room temperature
- each 5 mL contains: sodium 2 mg

Inactive ingredients

Carboxymethylcellulose, Flavor, Glycerin, High Fructose Corn Syrup, Methyl Paraben, Microcrystal Cellulose, Polyethylene Glycol 1450, Propyl Paraben, Propylene Glycol, Purified Water, Saccharin Sodium, Sorbitol, Sucralose, Xanthan Gum

Questions or comments?

1-732-249-6363

DISTRIBUTED BY
CHAIN DRUG CONSORTIUM
3301 NW BOCA RATON BLVD
SUITE 101, BOCA RATON, FL 33431

PRINCIPAL DISPLAY PANEL - 59 mL Bottle Label

NDC 68016-160-02

Premier
Value ®

Infants'
Pain Relief

PAIN RELIEVER - FEVER REDUCER
ACETAMINOPHEN

SUSPENSION LIQUID
• Dye Free
• Alcohol Free
• Aspirin Free

Use only with
enclosed syringe

Cherry Flavor

INDEPENDENTLY TESTED
PV
SATISFACTION GUARANTEED

2 FL OZ (59 mL)